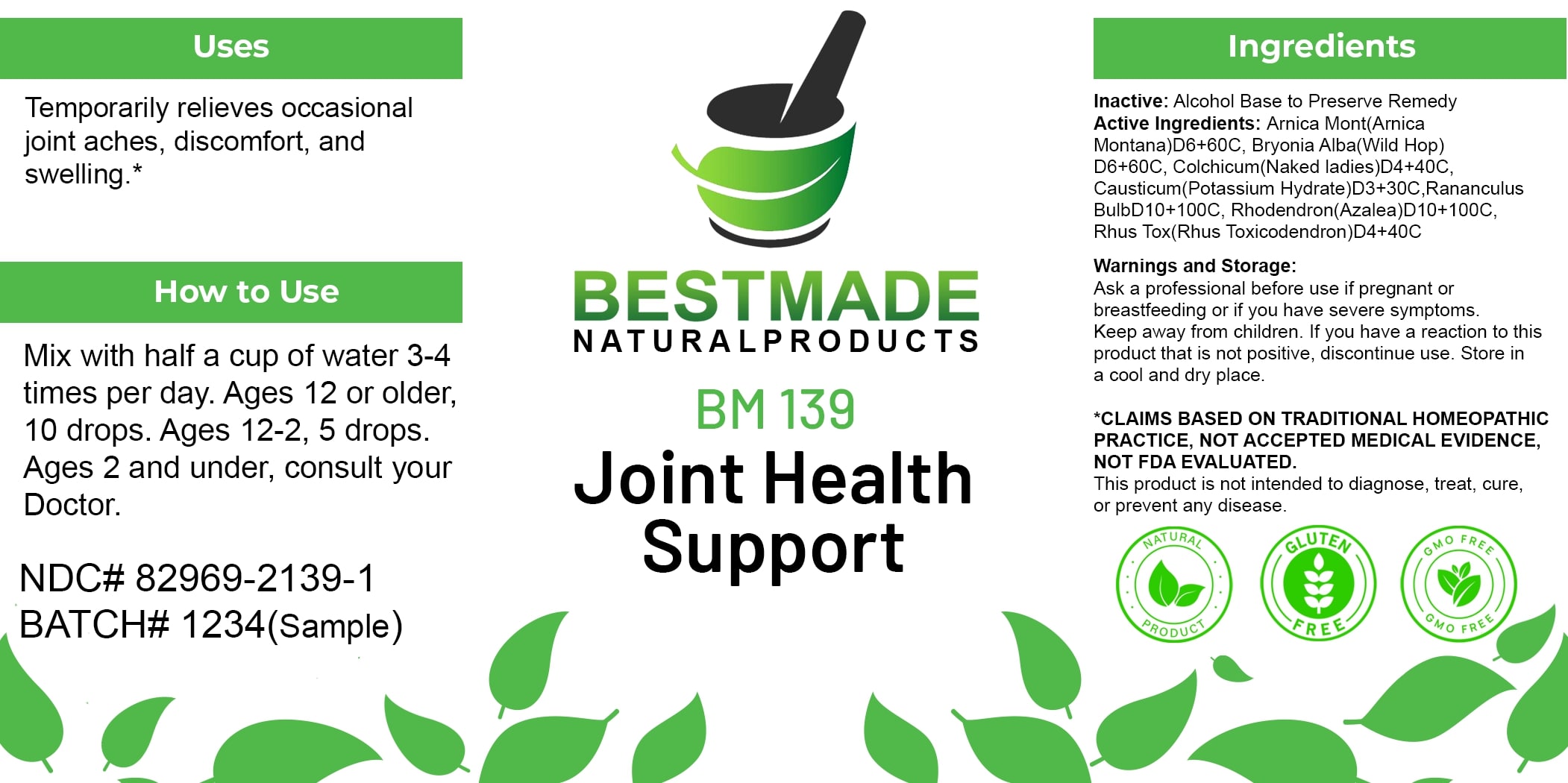 DRUG LABEL: Bestmade Natural Products BM139
NDC: 82969-2139 | Form: LIQUID
Manufacturer: Bestmade Natural Products
Category: homeopathic | Type: HUMAN OTC DRUG LABEL
Date: 20250214

ACTIVE INGREDIENTS: RHODODENDRON AUREUM LEAF 30 [hp_C]/30 [hp_C]; BRYONIA ALBA ROOT 30 [hp_C]/30 [hp_C]; ARNICA MONTANA 30 [hp_C]/30 [hp_C]; CAUSTICUM 30 [hp_C]/30 [hp_C]; TOXICODENDRON PUBESCENS LEAF 30 [hp_C]/30 [hp_C]; RANUNCULUS BULBOSUS WHOLE 30 [hp_C]/30 [hp_C]; COLCHICUM AUTUMNALE BULB 30 [hp_C]/30 [hp_C]
INACTIVE INGREDIENTS: ALCOHOL 30 [hp_C]/30 [hp_C]

BM139

DOSAGE AND ADMINISTRATION

How to Use

Mix with half a cup of water 3-4 times per day. Ages 12 or older, 10 drops. Ages 12-2, 5 drops. Ages 2 and under, consult your Doctor.

INACTIVE INGREDIENT

Ingredients

Inactive: Alcohol Base to Preserve Remedy

ACTIVE INGREDIENT

Active Ingredients: Arnica Mont(Arnica Montana)D6+60C, Bryonia Alba(Wild Hop) D6+60C, Colchicum(Naked ladies)D4+40C, Causticum(Potassium Hydrate)D3+30C, Ranunculus BulbD10+100C, Rhododendron(Azalea)D10+100C, Rhus Tox(Rhus Toxicodendron)D4+40C

Uses

Temporarily relieves occasional joint aches, discomfort, and swelling.*

*CLAIMS BASED ON TRADITIONAL HOMEOPATHIC PRACTICE, NOT ACCEPTED MEDICAL EVIDENCE. NOT FDA EVALUATED.

This product is not intended to diagnose, treat, cure, or prevent any disease.

Uses

Temporarily relieves occasional joint aches, discomfort, and swelling.*

*CLAIMS BASED ON TRADITIONAL HOMEOPATHIC PRACTICE, NOT ACCEPTED MEDICAL EVIDENCE. NOT FDA EVALUATED.

This product is not intended to diagnose, treat, cure, or prevent any disease.

KEEP OUT OF REACH OF CHILDREN

Warnings and Storage:

Ask a professional before use if pregnant or breastfeeding or if you have severe symptoms. Keep away from children. If you have a reaction to this product that is not positive, discontinue use. Store in a cool and dry place.

Warnings and Storage:

Ask a professional before use if pregnant or breastfeeding or if you have severe symptoms. Keep away from children. If you have a reaction to this product that is not positive, discontinue use. Store in a cool and dry place.

*CLAIMS BASED ON TRADITIONAL HOMEOPATHIC PRACTICE, NOT ACCEPTED MEDICAL EVIDENCE. NOT FDA EVALUATED.

This product is not intended to diagnose, treat, cure, or prevent any disease.

Entire package label